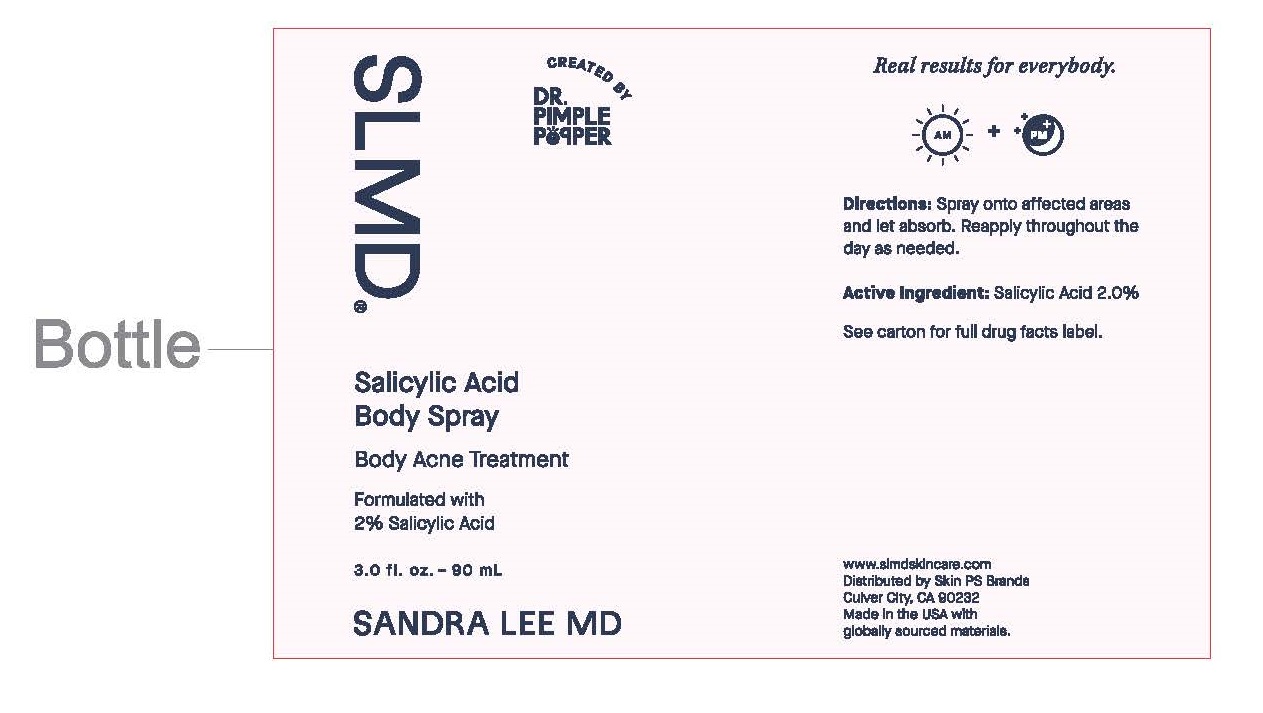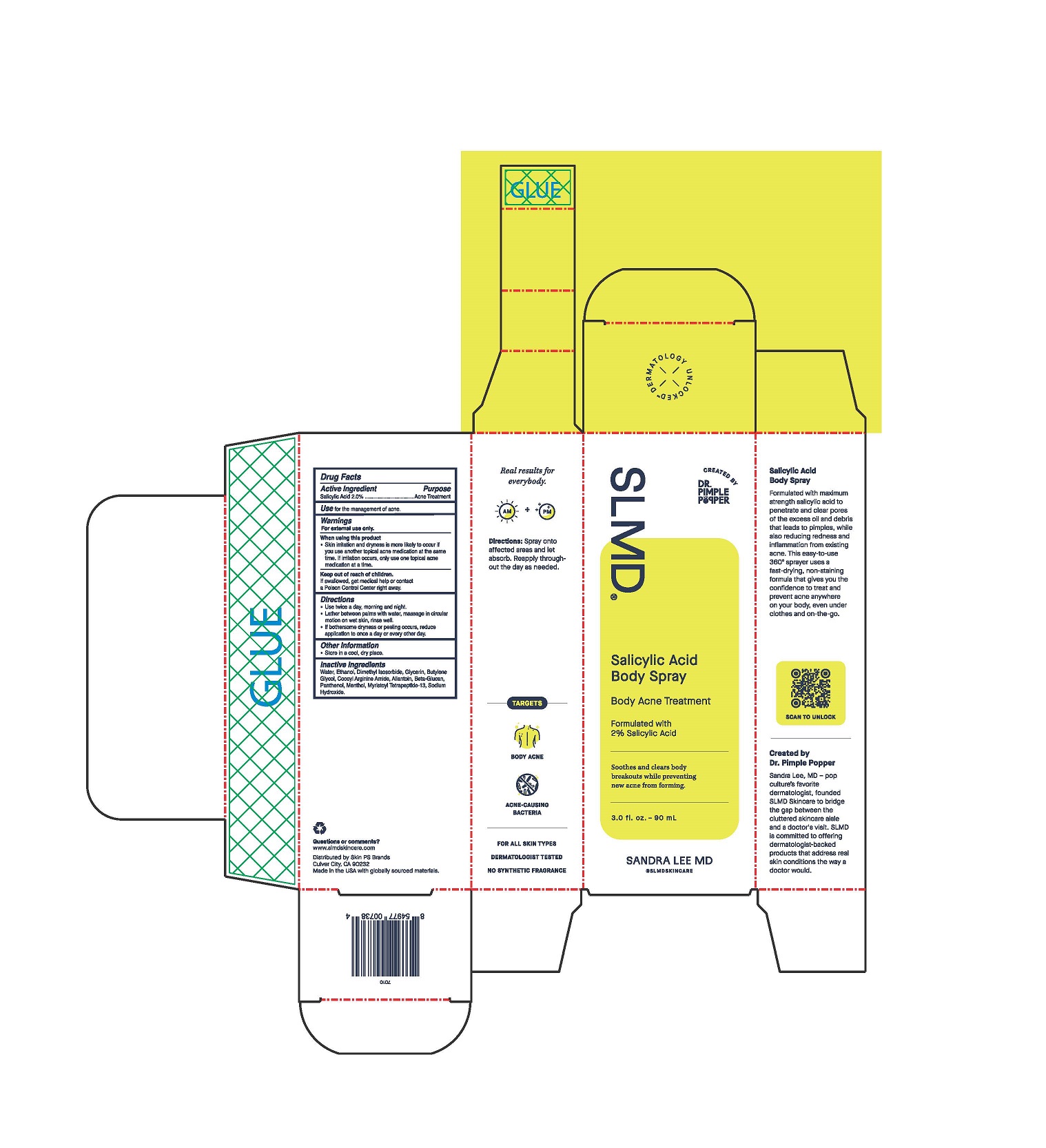 DRUG LABEL: Body Acne Treatment
NDC: 73318-7007 | Form: SPRAY
Manufacturer: Skin PS Brands
Category: otc | Type: HUMAN OTC DRUG LABEL
Date: 20251230

ACTIVE INGREDIENTS: SALICYLIC ACID 20 mg/1 g
INACTIVE INGREDIENTS: SODIUM HYDROXIDE; GLYCERIN; WATER; ALCOHOL; DIMETHYL ISOSORBIDE; BUTYLENE GLYCOL; ARGININE; ALLANTOIN; SODIUM CARBOXYMETHYL .BETA.-GLUCAN (DS 0.65-0.85); PANTHENOL; MENTHOL; MYRISTOYL TETRAPEPTIDE-4

Salicylic Acid Body Spray

Drug Facts

Salicylic Acid 2.0%

Purpose

Acne Treatment

Use

for the management of body acne.

Warnings

For external use only.

When using this product

- Skin irritation and dryness is more likely to occur if you use another topical acne medication at the same time. If irritation occurs, only use one topical acne medication at a time.

Keep out of reach of children.

If swallowed, get medical help or contact a Poison Control Center right away.

Directions

- Use twice a day, morning and night.
- Lather between palms with water, massage in a circular motion on wet skin, rinse well.
- If bothersome dryness or peeling occurs, reduce application to once a day or every other day.

Other information

- store in a cool, dry place

Inactive Ingredients

Water, Ethanol, Dimethyl Isosorbide, Glycerin, Butylene Glycol, Cocoyl Arginine Amide, Allantoin, Beta-Glucan, Panthenol, Menthol, Myristol Tetrapeptide-13, Sodium Hydroxide.

Questions or comments?

www.slmdskincare.com

Distributed by Skin PS Brands

Culver City, CA 90232

Made in the USA with globally courced materials.

SLMD

CREATED BY

DR. PIMPLE POPPER

Salicylic Acid Body Spray

Body Acne Treatment

Formulated with 2% Salicylic Acid

Soothes and clears body breakouts while preventing new acne from forming.

3.0 fl. oz. / 90 mL

SANDRA LEE MD

@SLMDSKINCARE

Salicylic Acid Body Spray

Formulated with maximum strength salicylic acid to penetrate and clear pores of the excess oil and debris that leads to pimples, while also reducing redness and inflammation from existing acne. This easy-to-use 360º sprayer uses a fast-drying, non-staining formula that gives you the confidence to treat and prevent acne anywhere on your body, even under clothes and on-the-go.

Created by Dr. Pimple Popper

Sandre Lee, MD - pop colture's favorite dermatologist - founded SLMD Skincare to bridge the gap between the cluttered skincare aisle and a doctor's visit. SLMD is committed to offering dermatologist-backed products that address real skin conditions the way a doctor would.

Real results for everybody.

AM + PM

Directions: Spray onto affected areas and let absorb. Reapply throughout the day, as needed.

TARGETS

BODY ACNE

ACNE-CAUSING BACTERIA

FOR ALL SKIN TYPES

DERMATOLOGIST TESTED

NO SYNTHETIC FRAGRANCE

Unit Carton

Primary